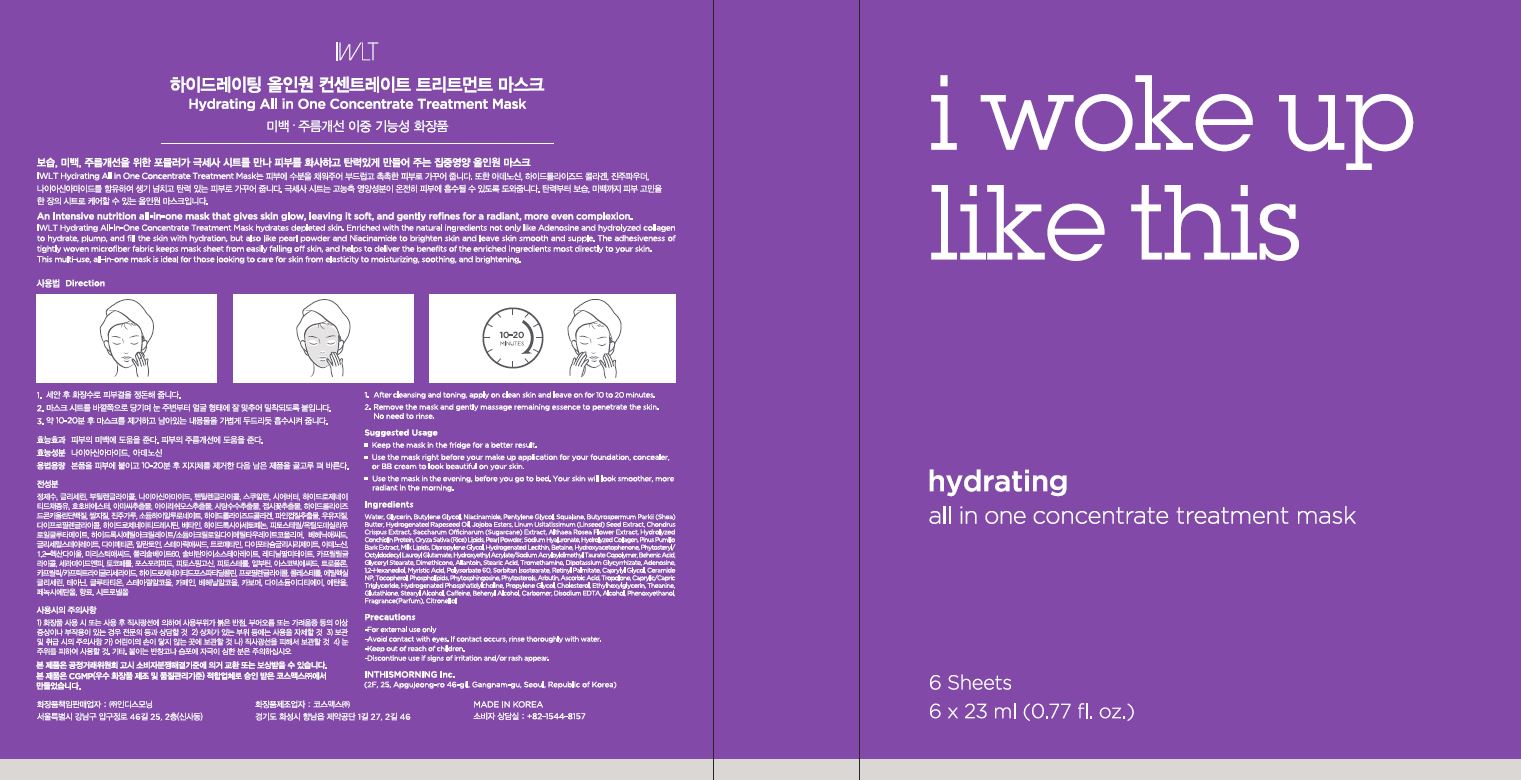 DRUG LABEL: Hydrating all in one concentrate treatment mask
NDC: 71217-0050 | Form: LIQUID
Manufacturer: inthismorning co ltd
Category: otc | Type: HUMAN OTC DRUG LABEL
Date: 20230129

ACTIVE INGREDIENTS: ADENOSINE 0.04 g/100 mL; NIACINAMIDE 2 g/100 mL
INACTIVE INGREDIENTS: WATER; GLYCERIN

Drug Facts

ACTIVE INGREDIENT

adenosine, niacinamide

INACTIVE INGREDIENT

water, glycerin, etc

PURPOSE

moisturizing, whitening, wrinkle care

keep out or reach of the children

INDICATIONS AND USAGE

1 after cleansing and toning, apply on clean skin and leave on for 10 to 20 minutes

2 remove the mask and gently massage remaining essence to penetrate the skin. no need to rinse

WARNINGS

This product is for exeternal use only. Do not use for internal use
Storage and handling precautions
If possible, avoid direct sunlight and store in cool and area of low humidity in order to maintain the quality of the product and avoid misuse
Avoid placing the product near fire and store out in reach of children

- consult a physician in case of abnormal symptoms, such as red spots, swelling or itching, or side effects in the areas of application due to direct light during or after using the product

- do not use on wounded area

DOSAGE AND ADMINISTRATION

for external use only